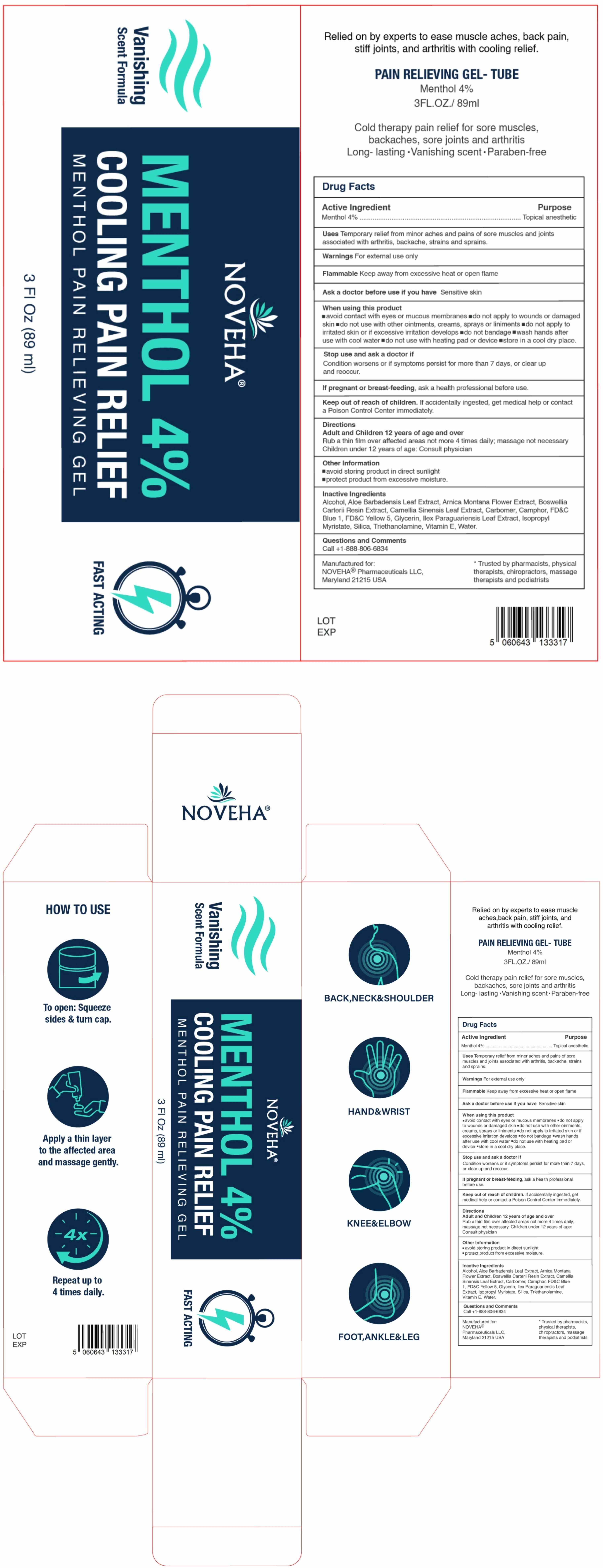 DRUG LABEL: Pain Relief Gel-Tube
NDC: 84008-003 | Form: GEL
Manufacturer: Bullet point LLC
Category: otc | Type: HUMAN OTC DRUG LABEL
Date: 20251104

ACTIVE INGREDIENTS: MENTHOL 0.04 g/1 mL
INACTIVE INGREDIENTS: FD&C YELLOW NO. 5; TROLAMINE; SILICON DIOXIDE; ILEX PARAGUARIENSIS LEAF; WATER; ISOPROPYL MYRISTATE; ALOE VERA LEAF; .ALPHA.-TOCOPHEROL, D-; FRANKINCENSE; FD&C BLUE NO. 1; GREEN TEA LEAF; ARNICA MONTANA FLOWER; GLYCERIN; CAMPHOR (SYNTHETIC); ALCOHOL 95%; CARBOMER HOMOPOLYMER, UNSPECIFIED TYPE

Active Ingredient

Menthol 4.0% w/w ...... Purpose: Topical Analgesic

Purpose

(Menthol) Topical Analgesic

Warnings

For external use only

WARNINGS AND PRECAUTIONS

Flammable

• Keep away from fire or flame

Use

Temporary relief from minor aches and pains of sore muscles and joints associated with arthritis, backache, strains and sprains

When using this product

• Avoid contact with eyes or mucous membranes

• Do not apply to wounds or damaged skin

• Do not use with other ointments, creams, sprays, or liniments

• Do not apply to irritated skin or if excessive irritation develops

• Do not bandage

• Wash hands after use with cool water

• Do not use with a heating pad or device

• Store in a cool, dry place

Stop use if

• Condition worsens or if symptoms persist for more than 7 days, or clear up and recur.

Ask a doctor if

Condition worsens or if symptoms persist for more than 7 days. or clear up and reoccur.

If pregnant or breast-feeding

- Ask a health professional before use

Keep out of reach of children

If swallowed, get medical help or contact the Poison Control Center immediately.

Directions

Adults and children 12 years of age and over:

- Rub a thin film over affected areas not more than 4 times daily
- Massage not necessary

Children under 12 years old: Consult physician

Other Information

- Avoid storing the product in direct sunlight
- Protect the product from excessive moisture.

Inactive Ingredients
Alcohol, Aloe Barbadensis Leaf Extract, Arnica Montana Flower Extract, Boswellia Carterii Resin Extract, Camellia Sinensis Leaf Extract, Carbomer, Camphor, FD&C Blue 1, FD&C Yellow 5, Glycerin, Ilex Paraguariensis Leaf Extract, Isopropyl Myristate, Silica, Triethanolamine, Vitamin E, Water

Questions or Comments

Call +1-888-806-6834